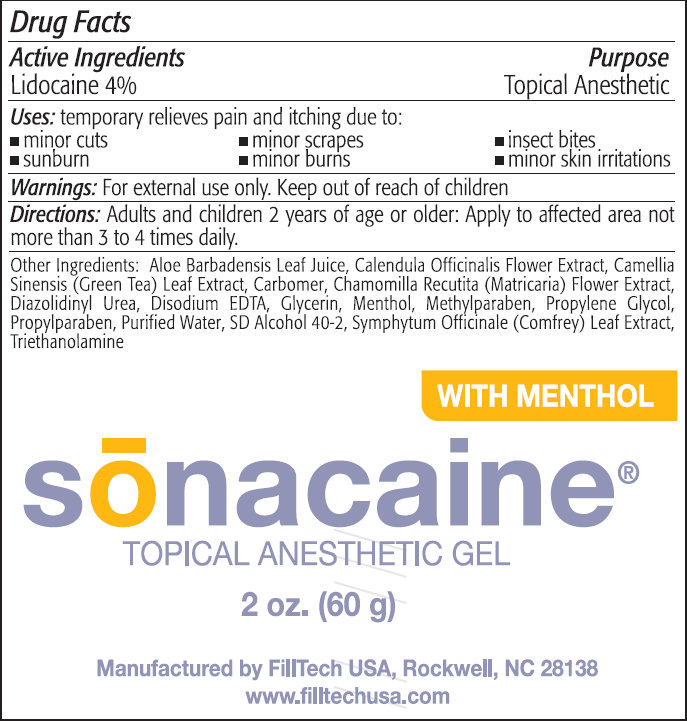 DRUG LABEL: Sonacaine Topical Anesthetic With Menthol
NDC: 62221-935 | Form: GEL
Manufacturer: Filltech USA, LLC
Category: otc | Type: HUMAN OTC DRUG LABEL
Date: 20231109

ACTIVE INGREDIENTS: LIDOCAINE 4 g/100 g
INACTIVE INGREDIENTS: ALOE VERA LEAF; CALENDULA OFFICINALIS FLOWER; GREEN TEA LEAF; CHAMOMILE; DIAZOLIDINYL UREA; EDETATE DISODIUM; GLYCERIN; MENTHOL; METHYLPARABEN; PROPYLENE GLYCOL; PROPYLPARABEN; WATER; ALCOHOL; COMFREY LEAF; TROLAMINE

Sonacaine Topical Anesthetic Gel With Menthol

Active Ingredients

Lidocaine 4%

Purpose

Topical Anesthetic

Uses:

temporary relieves pain and itching due to:

- minor cuts
- sunburn
- minor scrapes
- minor burns
- insect bites
- minor skin irritations

Warnings:

For external use only.

Directions:

Adults and children 2 years of age or older: Apply to affected area not more than 3 to 4 times daily.

Other Ingredients:

Aloe Barbadensis Leaf Juice, Calendula Officinalis Flower Extract, Camellia Sinensis (Green Tea) Leaf Extract, Carbomer, Chamomilla Recutita (Matricaria) Flower Extract, Diazolidinyl Urea, Disodium EDTA, Glycerin, Menthol, Methylparaben, Propylene Glycol, Propylparaben, Purified Water, SD Alcohol 40-2, Symphytum Officinale (Comfrey) Leaf Extract, Triethanolamine